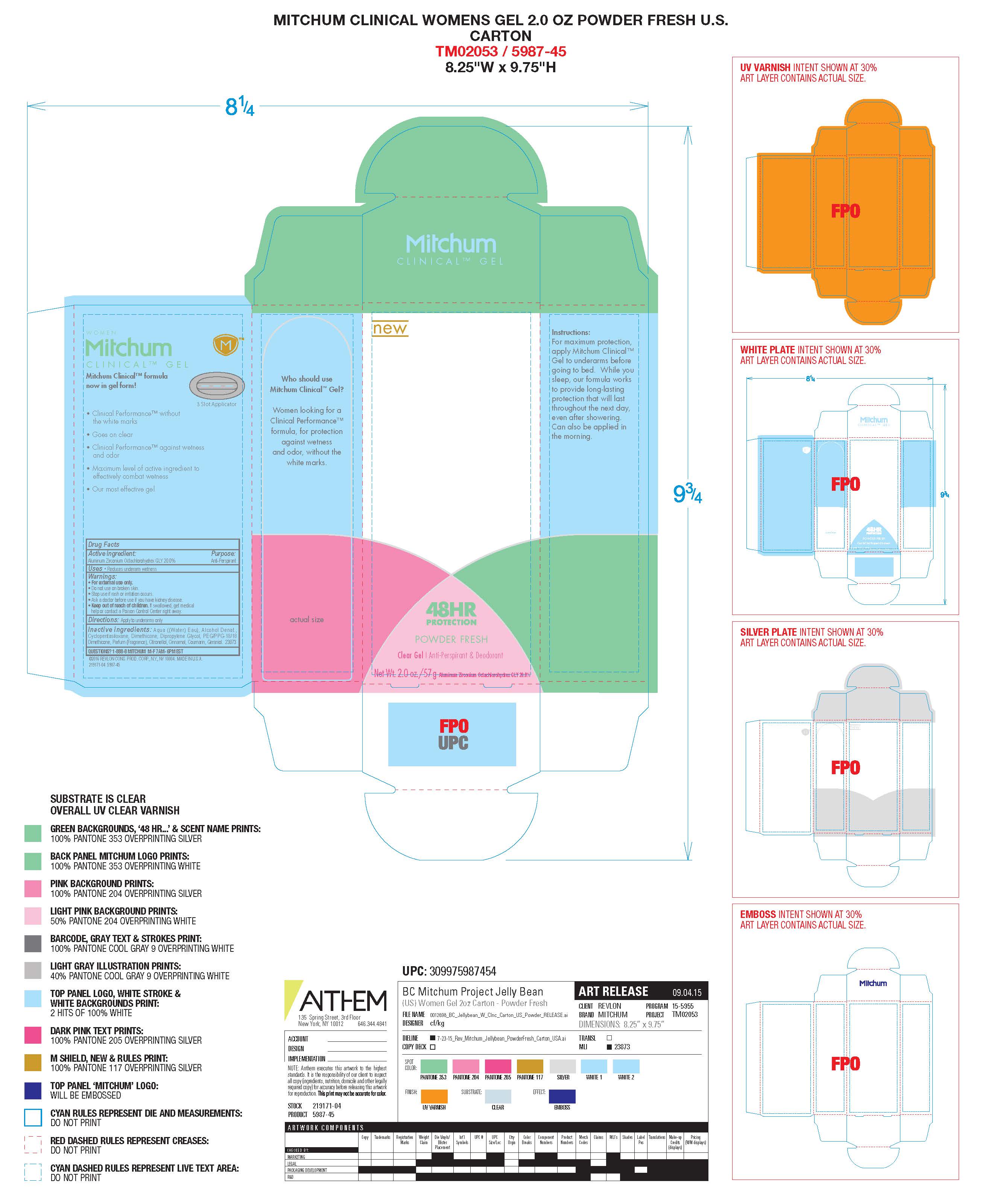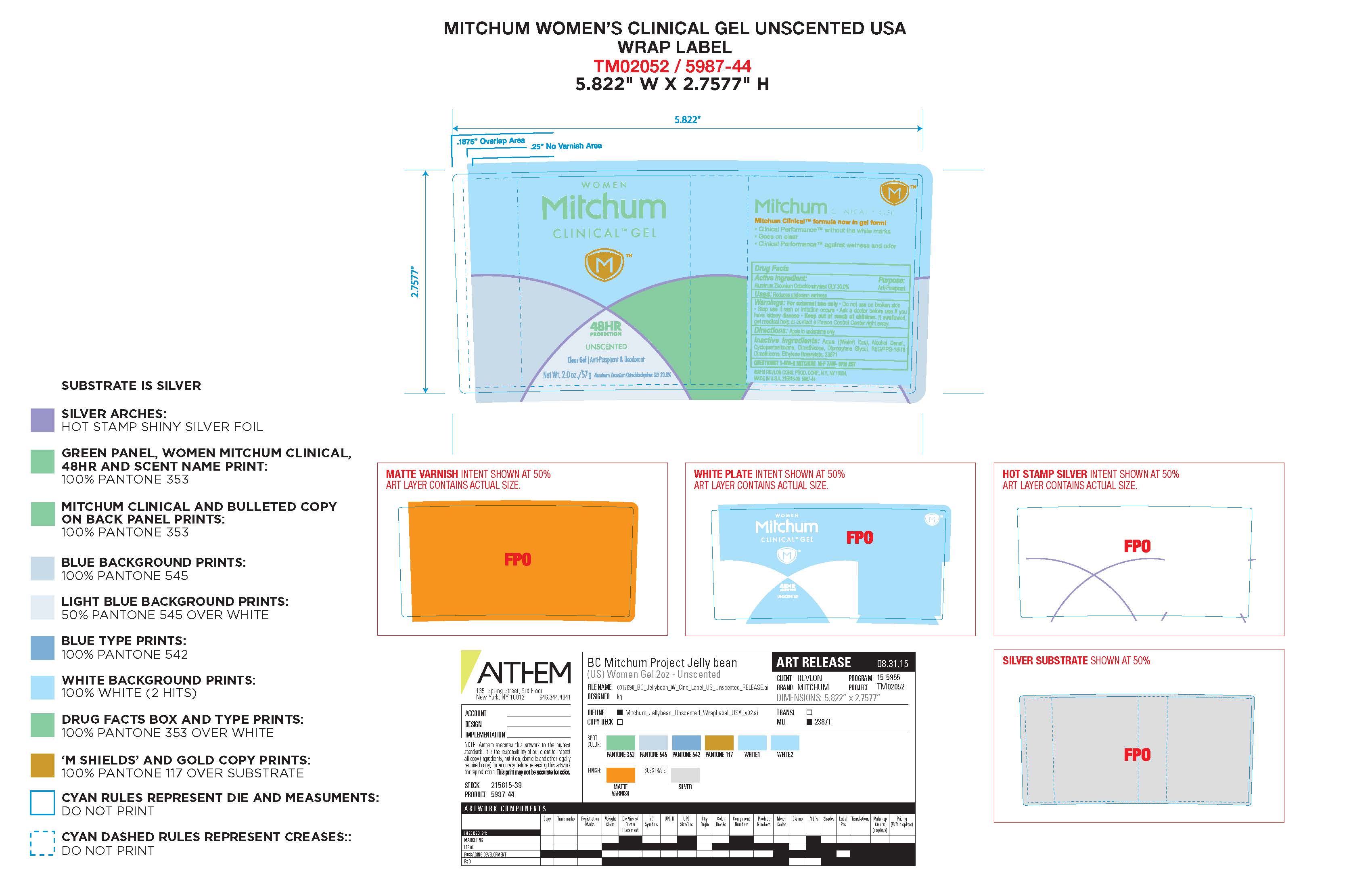 DRUG LABEL: Revlon Mitchum Clinical Gel
NDC: 10967-632 | Form: LIQUID
Manufacturer: Revlon Consumer Products Corp
Category: otc | Type: HUMAN OTC DRUG LABEL
Date: 20241231

ACTIVE INGREDIENTS: ALUMINUM ZIRCONIUM OCTACHLOROHYDREX GLY 0.2 g/1 mL
INACTIVE INGREDIENTS: WATER; ALCOHOL; DIMETHICONE; PEG/PPG-18/18 DIMETHICONE; COUMARIN; DIPROPYLENE GLYCOL; CYCLOMETHICONE 5; .BETA.-CITRONELLOL, (R)-; GERANIOL

Revlon Mitchum Clinical Gel

ACTIVE INGREDIENT

Aluminum Zirconium Octachlorohydrex Gly 20%

Purpose

Antiperspirant

Warnings:

For external use only.

Do not use on broken skin

Ask a doctor before use if you have kidney disease

Stop use if rash or irriation occurs

KEEP OUT OF REACH OF CHILDREN

If swallowed, get medical help or contact a Poison Control Center right away.

Inactive Ingredients

Aqua ((Water) Eau), Alcohol Denat., Cyclopentasiloxane, Dimethicone, Dipropylene Glycol, PEG/PPG-18/18 Dimethicone, Parfum (Fragrance), Citronellol, Cinnamal, Coumarin, Geraniol

INDICATIONS AND USAGE

Reduces underarm wetness

PACKAGE LABEL

Mitchum Roll On